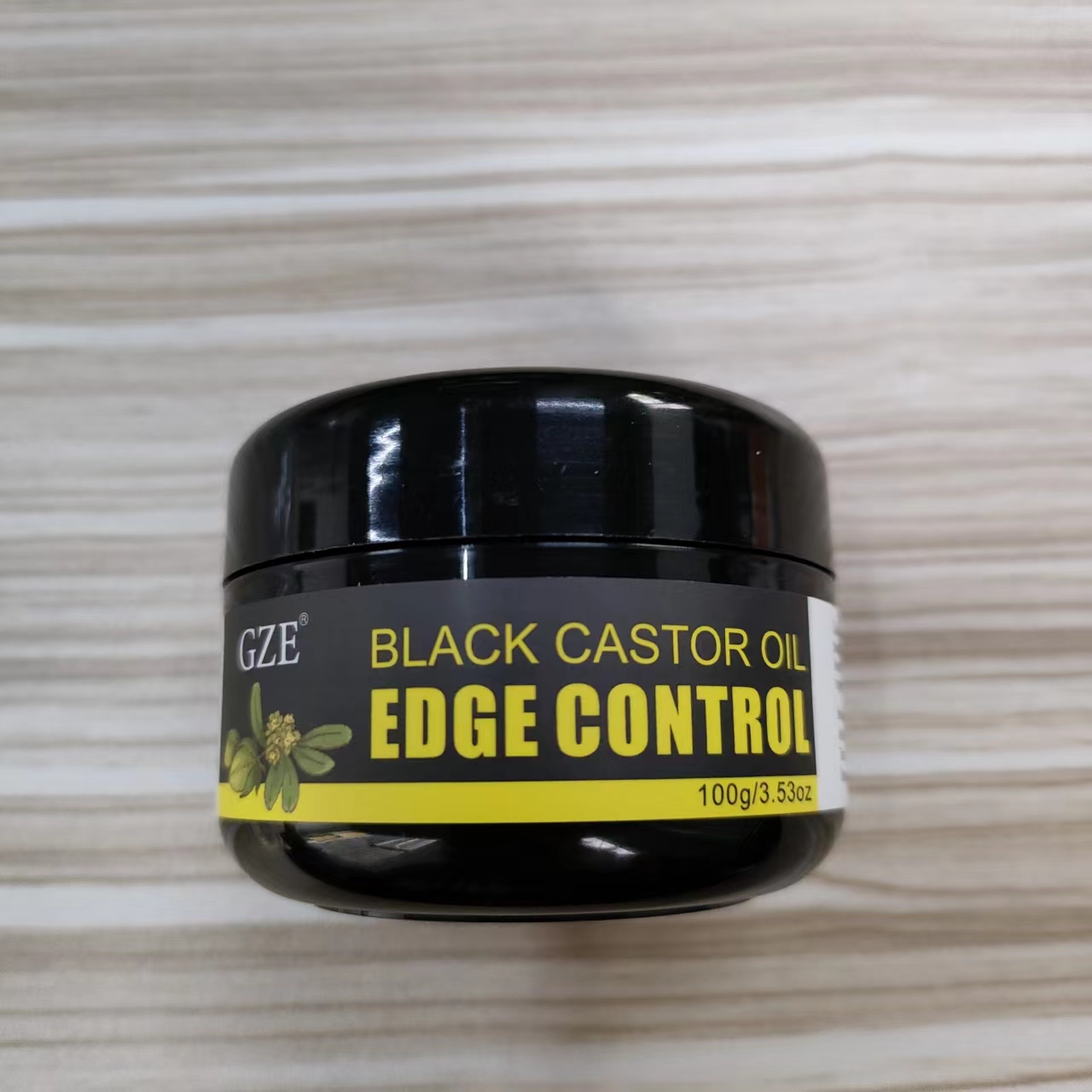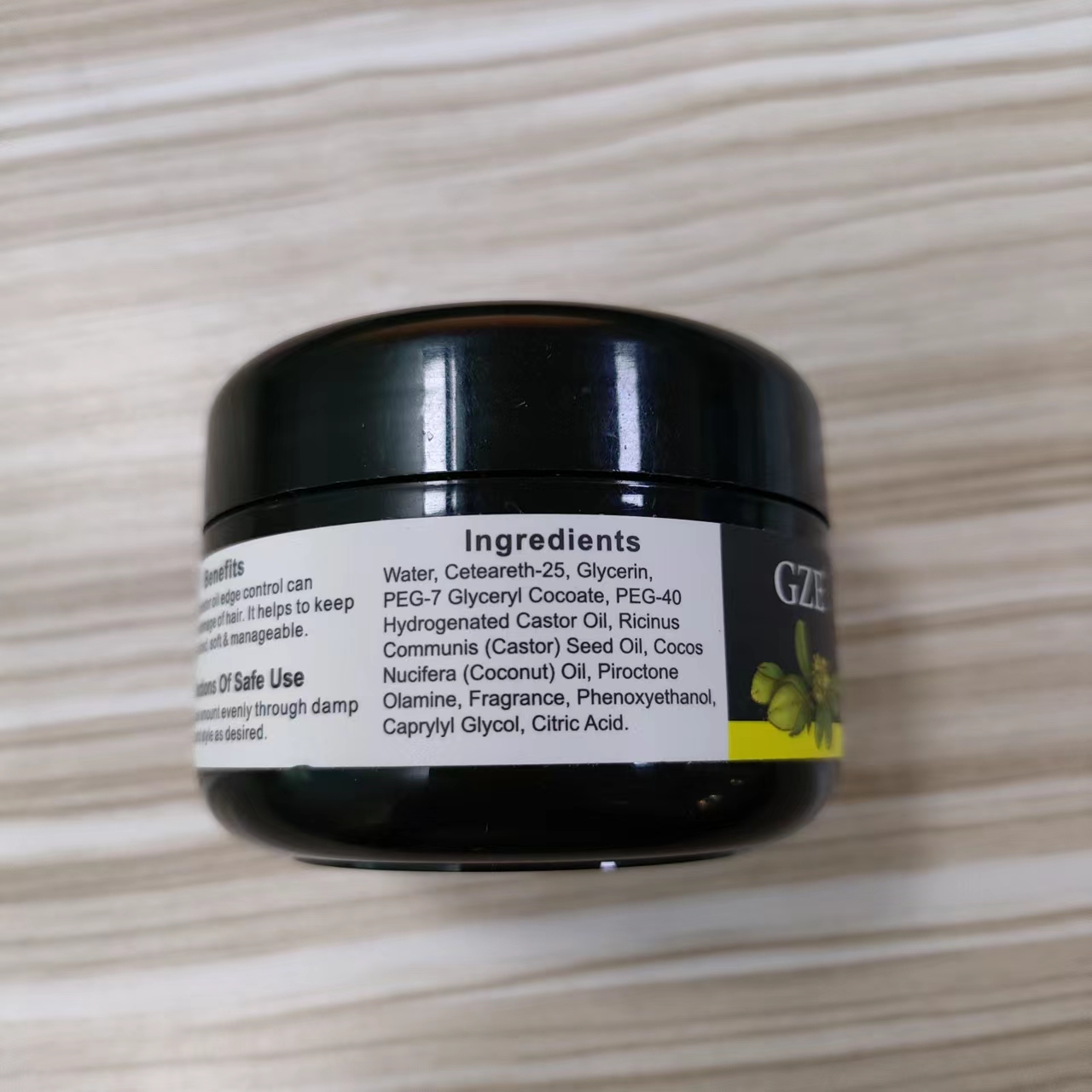 DRUG LABEL: GZE Black Castor Oil EdgeControl
NDC: 83566-189 | Form: GEL
Manufacturer: Guangzhou Yilong Cosmetics Co., Ltd
Category: otc | Type: HUMAN OTC DRUG LABEL
Date: 20240719

ACTIVE INGREDIENTS: PIROCTONE OLAMINE 4.4 g/100 g
INACTIVE INGREDIENTS: PEG-40 CASTOR OIL; RICINUS COMMUNIS SEED; PEG-7 GLYCERYL COCOATE; COCONUT OIL; WATER; CETEARETH-25; PHENOXYETHANOL; CITRIC ACID ACETATE; GLYCERIN; FRAGRANCE 13576; CAPRYLYL GLYCOL

GZE BLACK CASTOR OIL EDGE CONTROL

ACTIVE INGREDIENT

Piroctone Olamine

INACTIVE INGREDIENT

Water

Ceteareth-25

Glycerin

PEG-7 Glyceryl Cocoate

PEG-40 Hydrogenated Castor Oil

Ricinus Communis (Castor) Seed Oil

Cocos Nucifera (Coconut) Fruit Oil

Fragrance

Phenoxyethanol

Caprylyl Glycol

Citric Acid

PURPOSE

GZE black castor oil edge control can reduce the damage of hair. lt helps to keep hair moisturized, soft & manageable.

INDICATIONS AND USAGE

Apply a small amount evenly through damp or dry hair and style as desired.

Do not use on damaged or broken skin.

WARNINGS

For external use only.

Stop use and ask a doctor if rash occurs.

When using this product keep out of eyes. Rinse with water to remove.

Keep out of reach of children. If swallowed, get medical help or contact a Poison Control Center right away.

DOSAGE AND ADMINISTRATION

Apply a small amount evenly through damp or dry hair and style as desired.